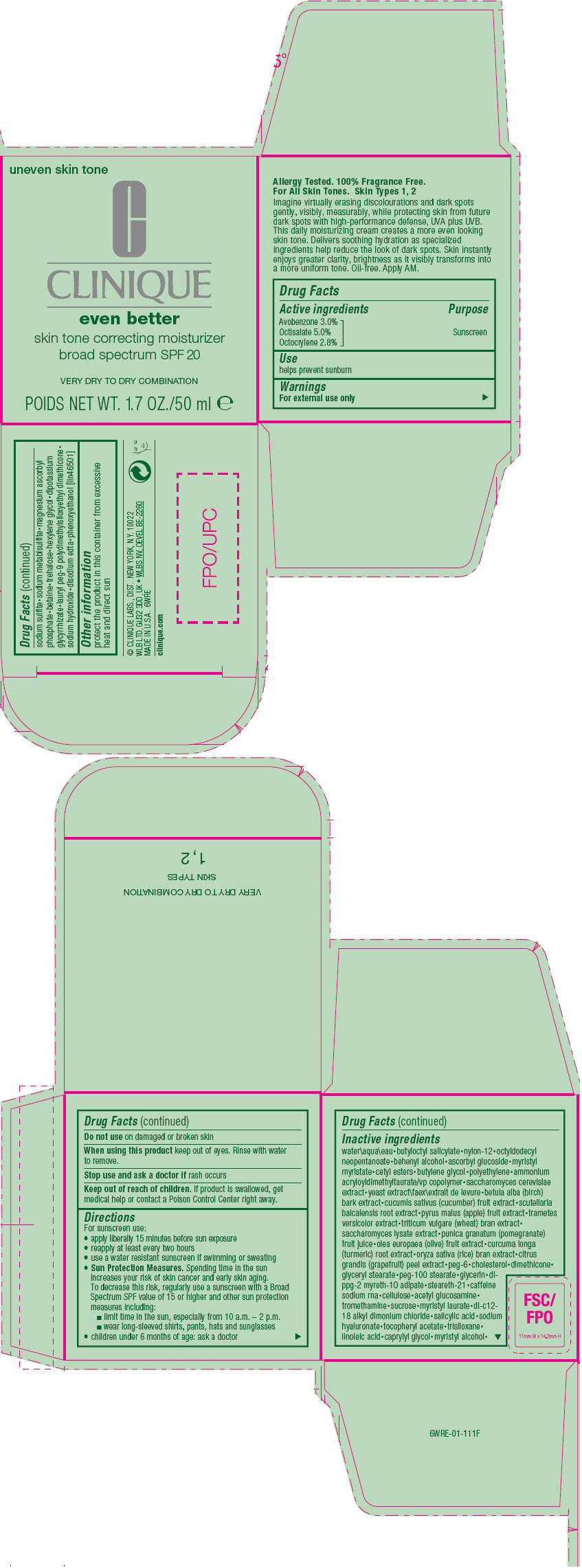 DRUG LABEL: EVEN BETTER SKIN TONE CORRECTING MOISTURIZER
NDC: 49527-082 | Form: CREAM
Manufacturer: CLINIQUE LABORATORIES LLC
Category: otc | Type: HUMAN OTC DRUG LABEL
Date: 20231020

ACTIVE INGREDIENTS: AVOBENZONE 30 mg/1 mL; OCTISALATE 50 mg/1 mL; OCTOCRYLENE 28 mg/1 mL
INACTIVE INGREDIENTS: WATER; BUTYLOCTYL SALICYLATE; NYLON-12; OCTYLDODECYL NEOPENTANOATE; ASCORBYL GLUCOSIDE; CETYL ESTERS WAX; BUTYLENE GLYCOL; HIGH DENSITY POLYETHYLENE; AMMONIUM ACRYLOYLDIMETHYLTAURATE/VP COPOLYMER; YEAST, UNSPECIFIED; BETULA PUBESCENS BARK; CUCUMBER; SCUTELLARIA BAICALENSIS ROOT; APPLE; WHEAT BRAN; SACCHAROMYCES LYSATE; POMEGRANATE JUICE; BLACK OLIVE; TURMERIC; RICE BRAN; CITRUS MAXIMA FRUIT RIND; POLYETHYLENE GLYCOL 300; CHOLESTEROL; DIMETHICONE; GLYCERYL MONOSTEARATE; PEG-100 STEARATE; GLYCERIN; STEARETH-21; CAFFEINE; POWDERED CELLULOSE; N-ACETYLGLUCOSAMINE; TROMETHAMINE; SUCROSE; SALICYLIC ACID; HYALURONATE SODIUM; .ALPHA.-TOCOPHEROL ACETATE; TRISILOXANE; LINOLEIC ACID; CAPRYLYL GLYCOL; SODIUM SULFITE; SODIUM METABISULFITE; MAGNESIUM ASCORBYL PHOSPHATE; BETAINE; TREHALOSE; HEXYLENE GLYCOL; GLYCYRRHIZINATE DIPOTASSIUM; LAURYL PEG-9 POLYDIMETHYLSILOXYETHYL DIMETHICONE; SODIUM HYDROXIDE; EDETATE DISODIUM; PHENOXYETHANOL; MYRISTYL ALCOHOL; N-DIALKYL METHYL BENZYL AMMONIUM CHLORIDE (C12-C18); MYRISTYL LAURATE; SODIUM RICINOLEATE; DI-PPG-2 MYRETH-10 ADIPATE; TRAMETES VERSICOLOR STRAIN CM-101; SACCHAROMYCES CEREVISIAE; MYRISTYL MYRISTATE; DOCOSANOL

EVEN BETTER SKIN TONE CORRECTING MOISTURIZER
BROAD SPECTRUM SPF 20

Drug Facts

Active ingredients

Avobenzone 3.0%
Octisalate 5.0%
Octocrylene 2.7%

Purpose

Sunscreen

Use

helps prevent sunburn

Warnings

For external use only

Do not use on damaged or broken skin

When using this product keep out of eyes. Rinse with water to remove.

Stop use and ask a doctor if rash occurs

Keep out of reach of children. If product is swallowed, get medical help or contact a Poison Control Center right away.

Directions

For sunscreen use:

- apply liberally 15 minutes before sun exposure
- reapply at least every two hours
- use a water resistant sunscreen if swimming or sweating
- Sun Protection Measures. Spending time in the sun increases your risk of skin cancer and early skin aging. To decrease this risk, regularly use a sunscreen with a Broad Spectrum SPF value of 15 or higher and other sun protection measures including:
  - limit time in the sun, especially from 10 a.m. – 2 p.m.
  - wear long-sleeved shirts, pants, hats and sunglasses
- children under 6 months of age: ask a doctor

Inactive ingredients

water\aqua\eau•butyloctyl salicylate•nylon-12•octyldodecyl neopentanoate•behenyl alcohol•ascorbyl glucoside•myristyl myristate•cetyl esters•butylene glycol•polyethylene•ammonium acryloyldimethyltaurate/vp copolymer•saccharomyces cerevisiae extract•yeast extract\faex\extrait de levure•betula alba (birch) bark extract•cucumis sativus (cucumber) fruit extract•scutellaria baicalensis root extract•pyrus malus (apple) fruit extract•trametes versicolor extract•triticum vulgare (wheat) bran extract•saccharomyces lysate extract•punica granatum (pomegranate) fruit juice•olea europaea (olive) fruit extract•curcuma longa (turmeric) root extract•oryza sativa (rice) bran extract•citrus grandis (grapefruit) peel extract•peg-6•cholesterol•dimethicone•glyceryl stearate•peg-100 stearate•glycerin•di-ppg-2 myreth-10 adipate•steareth-21•caffeine sodium rna•cellulose•acetyl glucosamine•tromethamine•sucrose•myristyl laurate•di-c12-18 alkyl dimonium chloride•salicylic acid•sodium hyaluronate•tocopheryl acetate•trisiloxane•linoleic acid•caprylyl glycol•myristyl alcohol•sodium sulfite•sodium metabisulfite•magnesium ascorbyl phosphate•betaine•trehalose•hexylene glycol•dipotassium glycyrrhizate•lauryl peg-9 polydimethylsiloxyethyl dimethicone•sodium hydroxide•disodium edta•phenoxyethanol [iln46501]

Other information

protect the product in this container from excessive heat and direct sun

CLINIQUE LABORATORIES, DIST. N.Y., N.Y. 10022
NEW YORK • LONDON W1K 3BQ • PARIS

PRINCIPAL DISPLAY PANEL - 50 mL Jar Carton

uneven skin tone

CLINIQUE
even better

skin tone correcting moisturizer
broad spectrum SPF 20

VERY DRY TO DRY COMBINATION

POIDS NET WT. 1.7 OZ./50 ml e